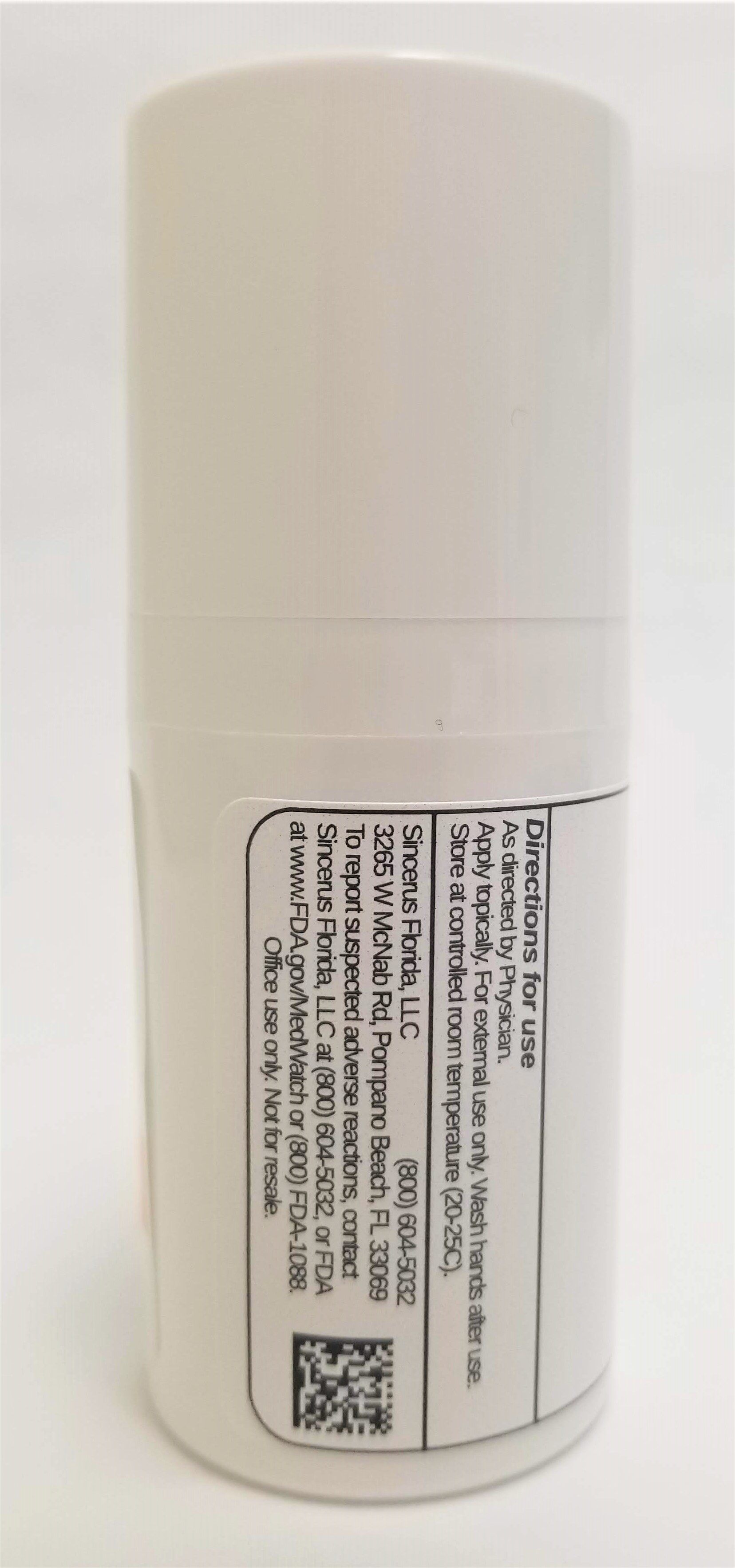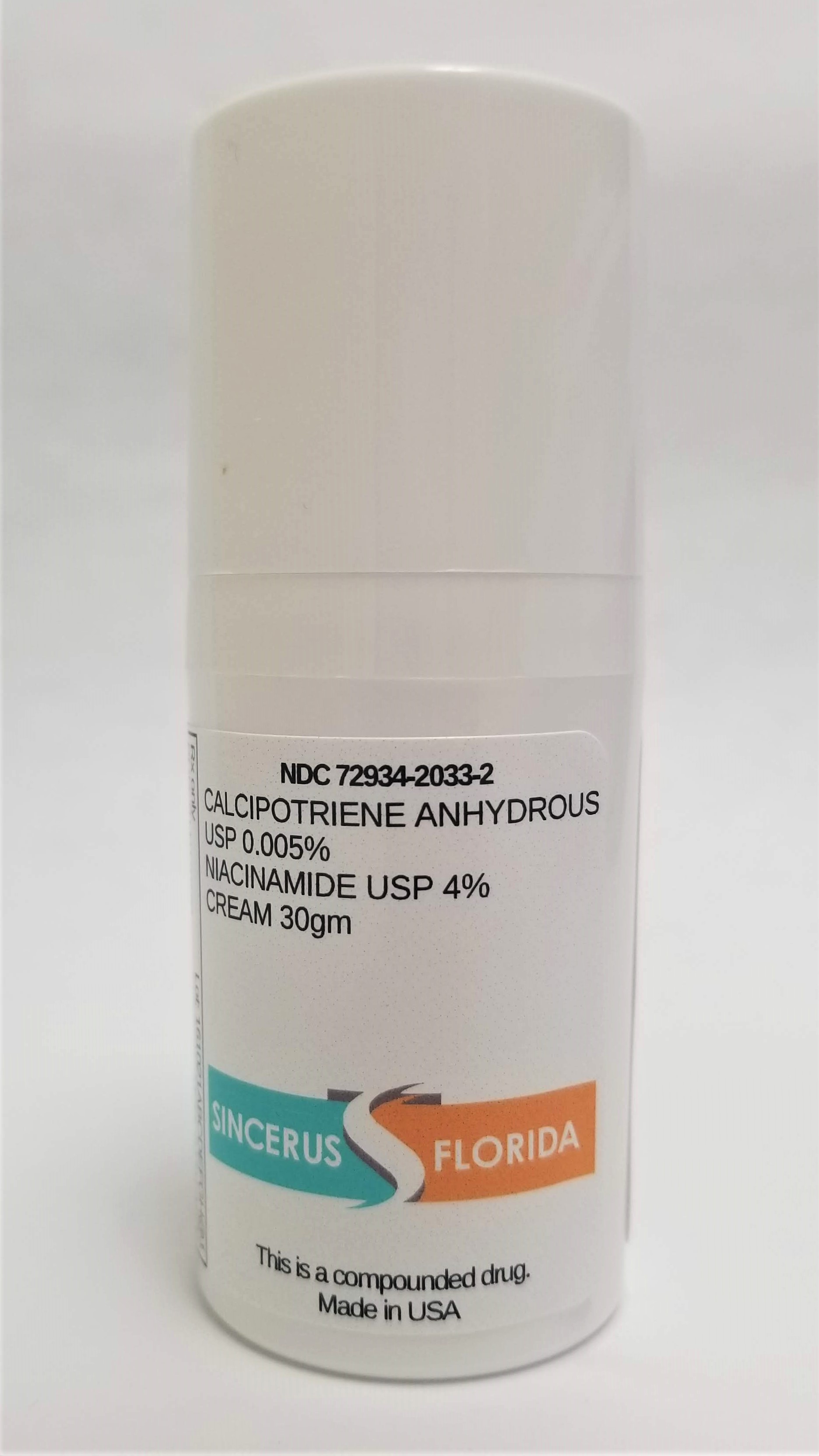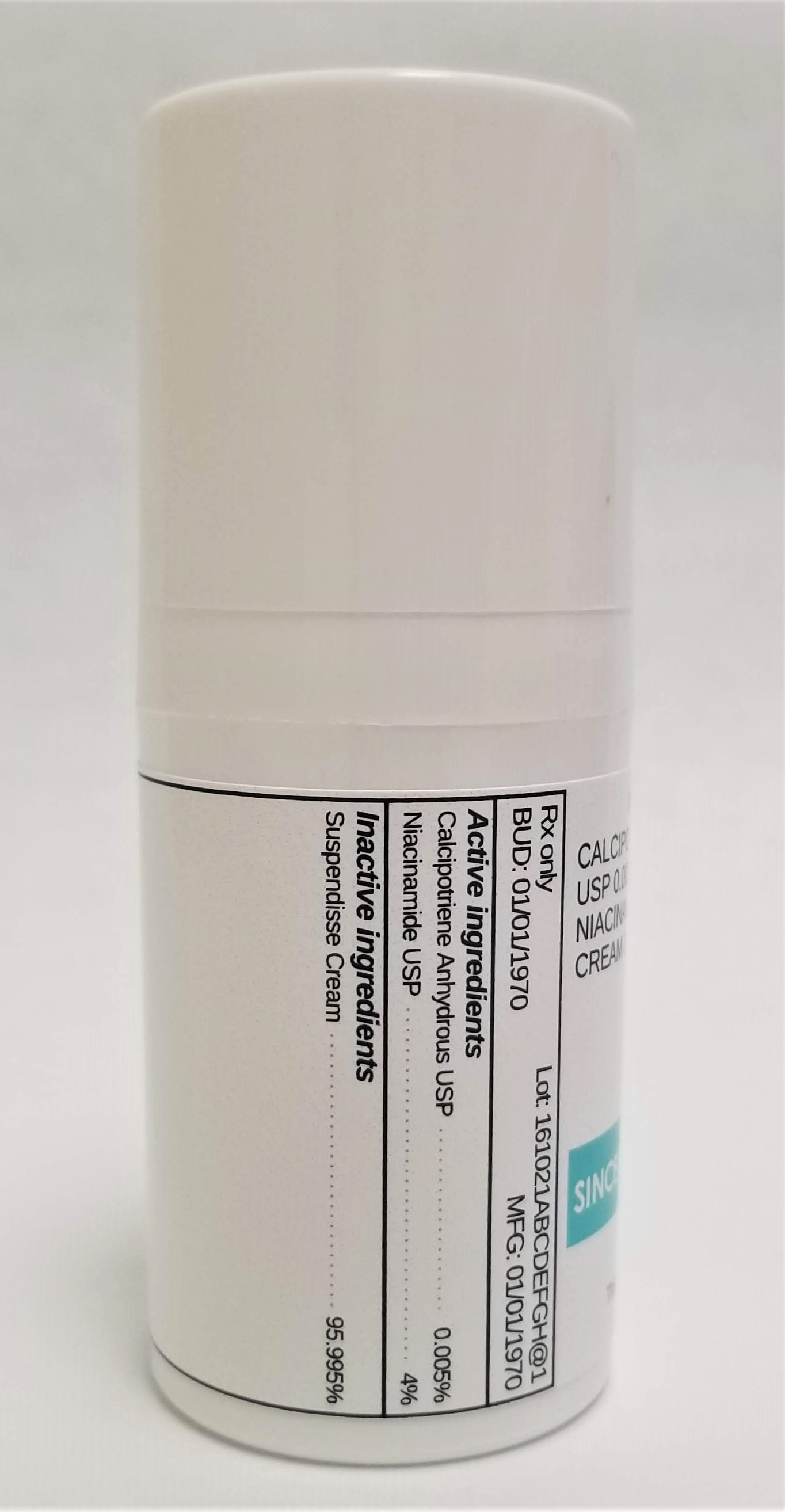 DRUG LABEL: CALCIPOTRIENE 0.005% / NIACINAMIDE 4%
NDC: 72934-2033 | Form: CREAM
Manufacturer: Sincerus Florida, LLC
Category: prescription | Type: HUMAN PRESCRIPTION DRUG LABEL
Date: 20190513

ACTIVE INGREDIENTS: NIACINAMIDE 4 g/100 g; CALCIPOTRIENE 0.005 g/100 g

CALCIPOTRIENE 0.005% / NIACINAMIDE 4%